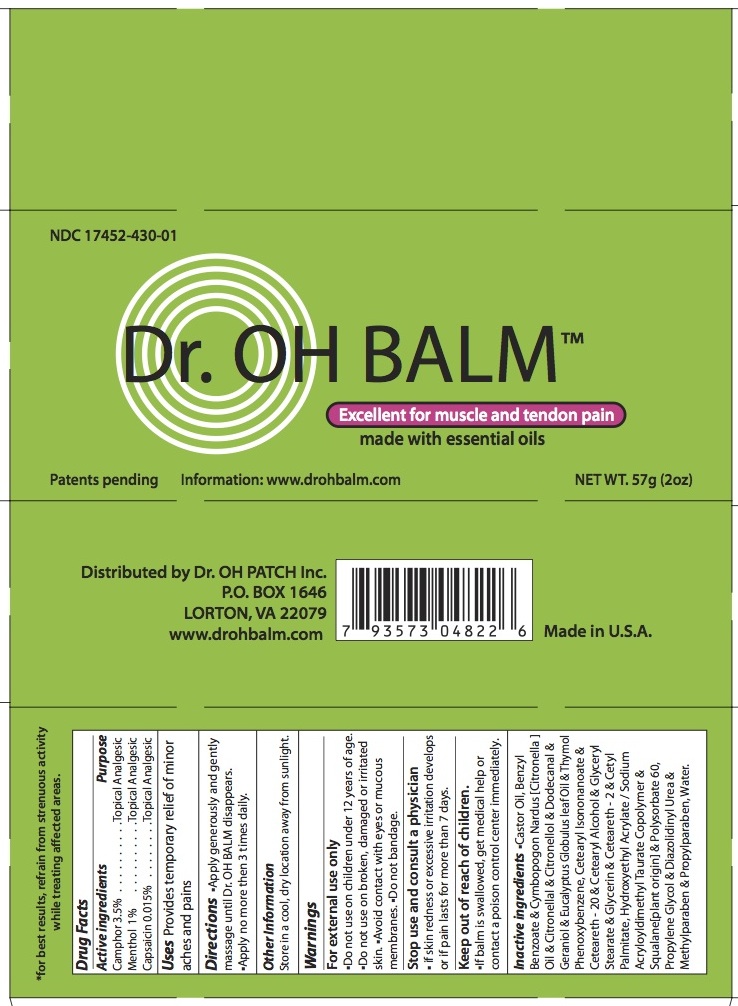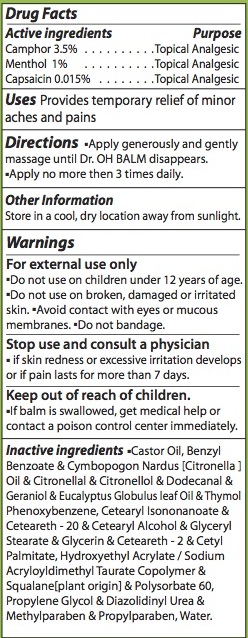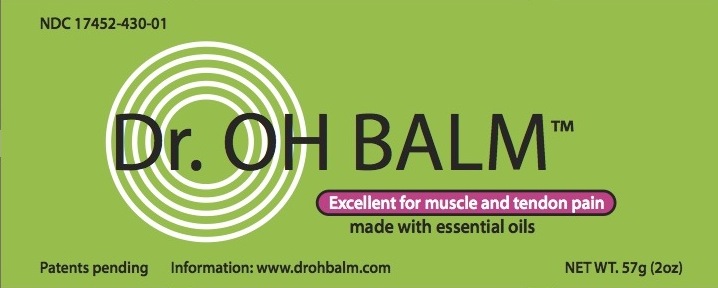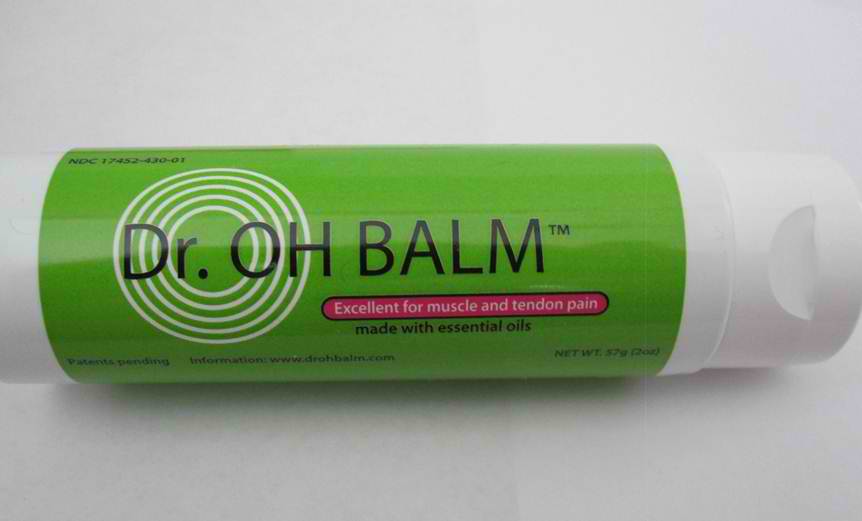 DRUG LABEL: Dr. OH BALM
NDC: 17452-430 | Form: CREAM
Manufacturer: Ecometics, Inc.
Category: otc | Type: HUMAN OTC DRUG LABEL
Date: 20120426

ACTIVE INGREDIENTS: MENTHOL 1 g/100 g; CAMPHOR (SYNTHETIC) 3.5 g/100 g; CAPSAICIN 0.015 g/100 g
INACTIVE INGREDIENTS: CASTOR OIL; BENZYL BENZOATE; CITRONELLA OIL; CITRONELLAL; .BETA.-CITRONELLOL, (R)-; LAURYL ALDEHYDE; GERANIOL; EUCALYPTUS OIL; THYMOL; CETEARYL ISONONANOATE; POLYOXYL 20 CETOSTEARYL ETHER; CETOSTEARYL ALCOHOL; GLYCERYL MONOSTEARATE; GLYCERIN; CETYL PALMITATE; SQUALANE; POLYSORBATE 60; PROPYLENE GLYCOL; DIAZOLIDINYL UREA; METHYLPARABEN; PROPYLPARABEN; BENZOPHENONE; WATER

Drug Facts

ACTIVE INGREDIENT

Camphor 3.5% .. Topical Analgesic
Menthol 1% .. Topical Analgesic
Capsaicin 0.015% .. Topical Analgesic

INACTIVE INGREDIENT

Benzyl Benzoate and Cymbopogon Nardus [ Citronella ] Oil and Citronellal and Citronellol
. . . and Dodecanal and Geraniol and Eucalyptus Globulus Leaf Oil and Thymol and Phenoxybenzene
Castor Oil
Cetearyl Isononanoate and Ceteareth - 20 and Cetearyl Alcohol and Glyceryl Stearate and Glycerin
. . . and Ceteareth - 2 and Cetyl Palmitate
Hydroxyethyl Acrylate / Sodium Acryloyldimethyl Taurate Copolymer and Squalane [ plant origin ] and Polysorbate 60
Propylene Glycol and Diazolidinyl Urea and Mehtylparaben and Propylparaben
Water

PACKAGE LABEL

NDC 17452-430-01
Dr. OH BALM (TM)
Excellent for muscle and tendon pain
made with essential oils
Patents pending
Information: www.drohbalm.com
NET WT. 57g (2oz)

WARNINGS

For external use only
Do not use on broken, damaged or irritated skin.
Avoid contact with eyes or mucous membranes.
Do not bandage.
Stop use and consult a physician,
if skin redness or excessive irritation develops or if pain last more than 7 days.
For best results, refrain from strenuous activity while treating affected.

PURPOSE

Topical analgesic. Provides temporary relief of minor aches and pains.

INDICATIONS AND USAGE

Apply generously and gently massage until Dr. OH BALM disappears.
Apply no more than 3 times daily.

Other Information: Store in a cool, dry location away from sunlight.
Distributed by
Dr. OH PATCH Inc.
P.O. BOX 1646
LORTON, VA 22079
www.drohbalm.com
Made in U.S.A.

Keep out of reach of children
Do not use on children under 12 years of age.
If balm is swallowed, get medical help or contact a poison control center immediately.

DOSAGE AND ADMINISTRATION

Apply generously and gently massage until Dr. OH BALM disappears.
Apply no more than 3 times daily.